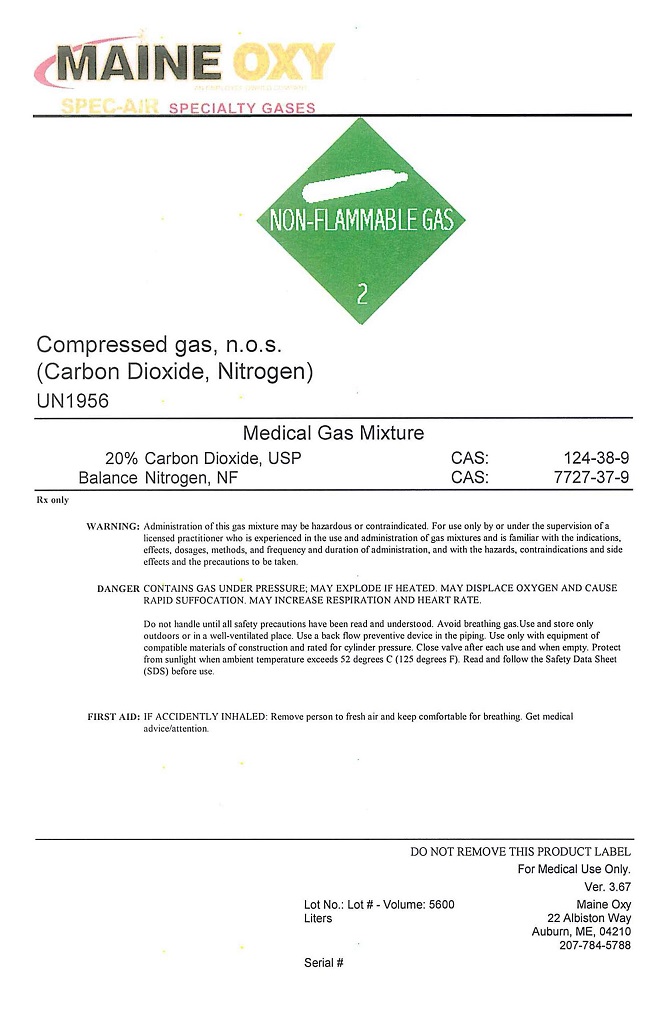 DRUG LABEL: Carbon Dioxide Nitrogen
NDC: 51887-302 | Form: GAS
Manufacturer: Maine Oxy-Acetylene Supply Company
Category: prescription | Type: HUMAN PRESCRIPTION DRUG LABEL
Date: 20251120

ACTIVE INGREDIENTS: CARBON DIOXIDE 200 mL/1 L
INACTIVE INGREDIENTS: NITROGEN 800 mL/1 L

Carbon Dioxide Nitrogen mix

PACKAGE LABEL

MAINE OXY SPEC-AIR SPECIALTY GASES
NON-FLAMMABLE GAS 2 Compressed Gas, n.o.s. (Carbon Dioxide, Nitrogen) UN1956
Medical Gas Mixture 20% Carbon Dioxide, USP CAS: 124-38-9 Balance Nitrogen, USP CAS: 7727-37-9
Rx only
WARNING: Administration of this gas mixture may be hazardous or contraindicated. For use only by or under the supervision of a licensed practitioner who is experienced in the use and administration of gas mixtures and is familiar with the indications, effects, dosages, methods, and frequency and duration of administration, and with the hazards, contraindications, and side effects and the precautions to be taken.
DANGER: CONTAINS GAS UNDER PRESSURE; MAY EXPLODE IF HEATED. MAY DISPLACE OXYGEN AND CAUSE RAPID SUFFOCATION. MAY INCREASE RESPIRATION AND HEART RATE.
Do not handle until all safety precautions have been read and understood. Keep and store away from clothing and other combustible materials. Keep valves and fittings free from grease and oil. Use and store only outdoors or in a well-ventilated place. In case of fire: Stop leak if safe to do so. Use a back flow preventive device in the piping. Use only with equipment of compatible materials of construction and rated for cylinder pressure. Use only with equipment cleaned for oxygen service. Open valve slowly. Close valve after each use and when empty. Protect from sunlight when Protect from sunlight when ambient temperature exceeds 52 degrees C (125 degrees F). Read and follow the Safety Data Sheet (SDS) before use.
FIRST AID: IF ACCIDENTLY INHALED: Remove person to fresh air and keep comfortable for breathing. Get medical advice/attention.
DO NOT REMOVE THIS PRODUCT LABEL
For Medical Use Only. Ver. 3.67 Lot No.: Lot# - Volume: 5600 Serial #
MAINE OXY 22 ALBISTON WAY . AUBURN, ME 04210 . 207-784-5788